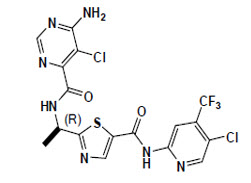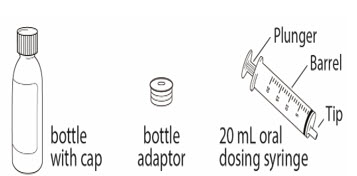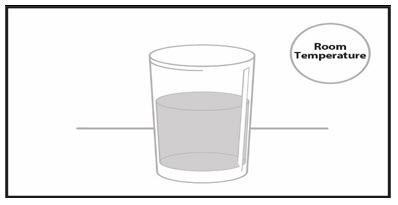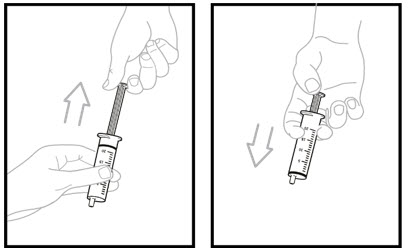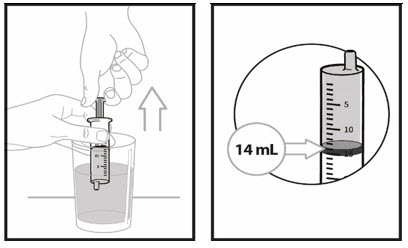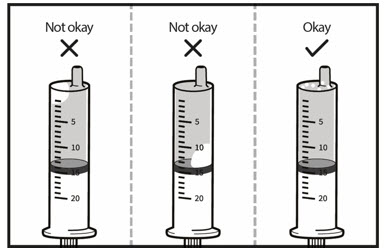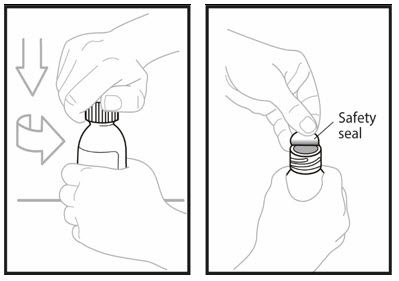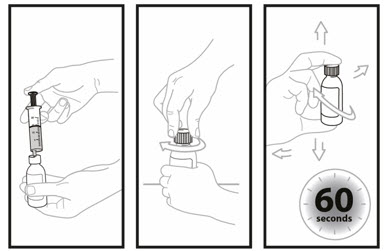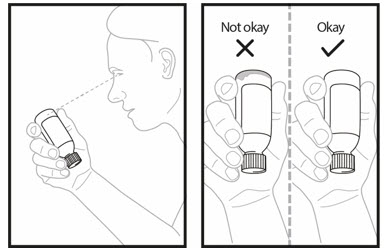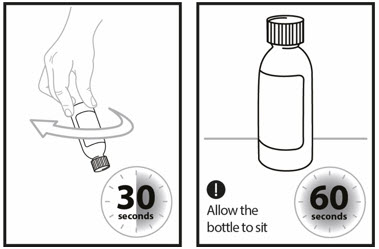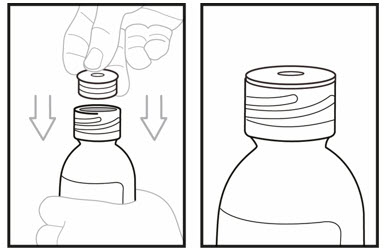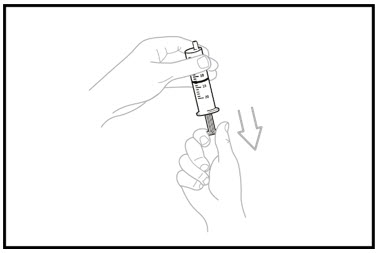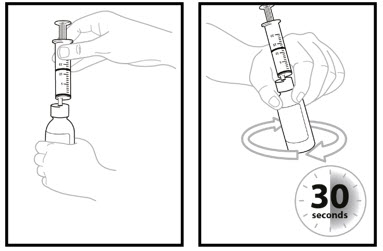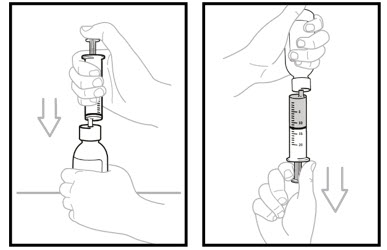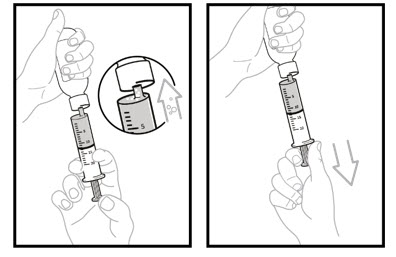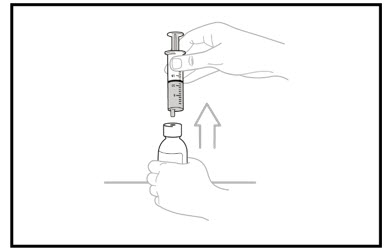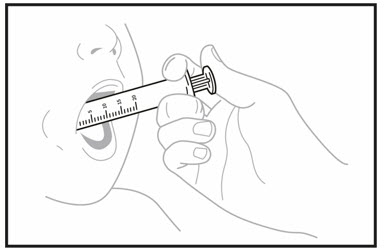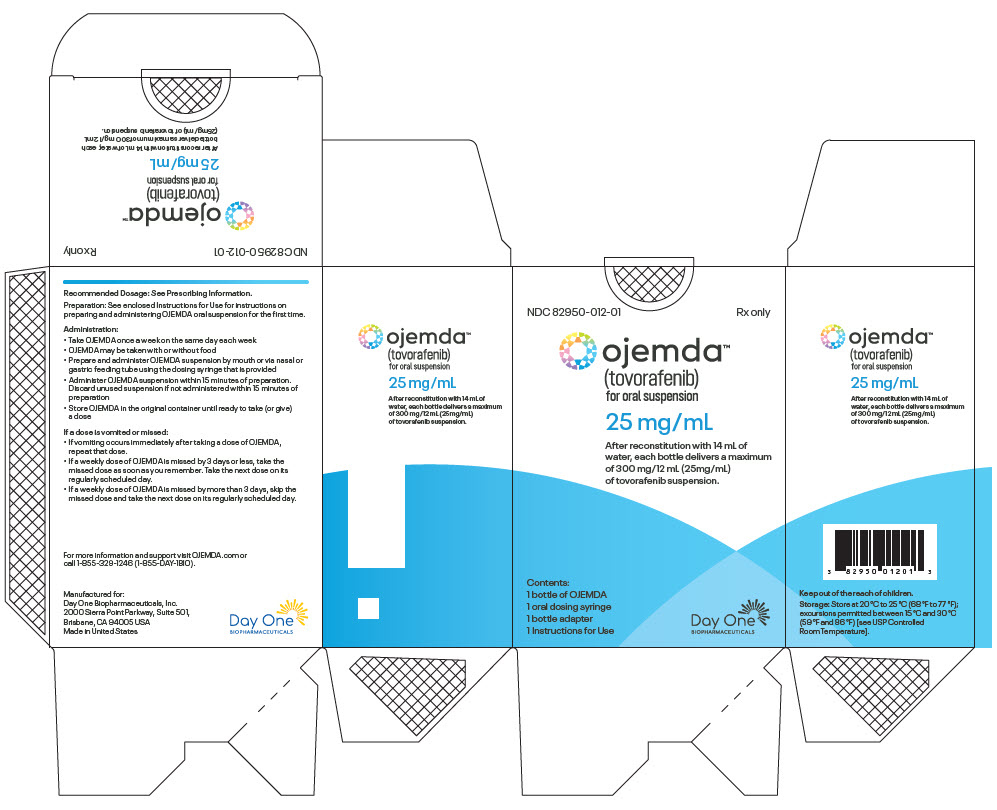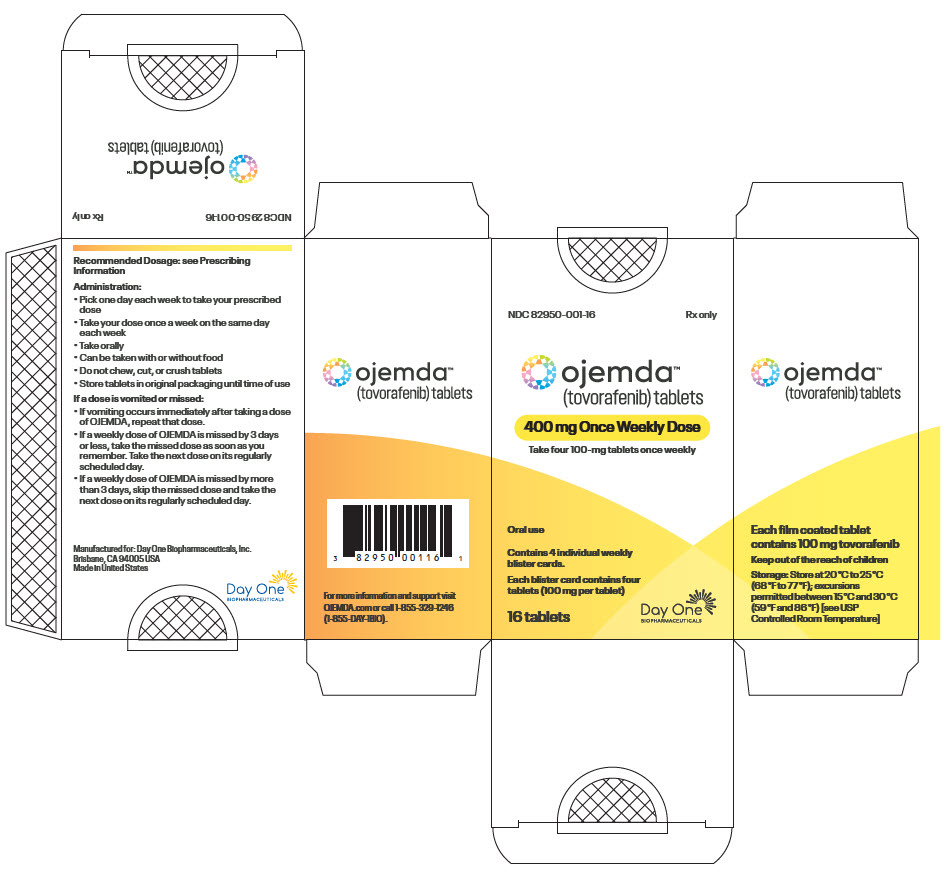 DRUG LABEL: OJEMDA
NDC: 82950-012 | Form: KIT | Route: ORAL
Manufacturer: Day One Biopharmaceuticals, Inc.
Category: prescription | Type: HUMAN PRESCRIPTION DRUG LABEL
Date: 20250902

ACTIVE INGREDIENTS: TOVORAFENIB 25 mg/1 mL
INACTIVE INGREDIENTS: MANNITOL; COPOVIDONE K25-31; SUCRALOSE; MALTODEXTRIN; SILICON DIOXIDE; MICROCRYSTALLINE CELLULOSE; SODIUM LAURYL SULFATE; DIMETHICONOL/TRIMETHYLSILOXYSILICATE CROSSPOLYMER (40/60 W/W; 1000000 PA.S)

HIGHLIGHTS OF PRESCRIBING INFORMATION

These highlights do not include all the information needed to use OJEMDA safely and effectively. See full prescribing information for OJEMDA.
OJEMDA (tovorafenib) tablets, for oral use
OJEMDA (tovorafenib) for oral suspension
Initial U.S. Approval: 2024

RECENT MAJOR CHANGES

Dosage and Administration (2.1) | 08/2025
Warnings and Precautions (5.4) | 08/2025

1 INDICATIONS AND USAGE

OJEMDA is a kinase inhibitor indicated for the treatment of patients 6 months of age and older with relapsed or refractory pediatric low-grade glioma (LGG) harboring a BRAF fusion or rearrangement, or BRAF V600 mutation. (1)

This indication is approved under accelerated approval based on response rate and duration of response [see Clinical Studies (14)]. Continued approval for this indication may be contingent upon verification and description of clinical benefit in a confirmatory trial(s).

2 DOSAGE AND ADMINISTRATION

- Confirm the presence of BRAF fusion or rearrangement, or BRAF V600 mutation prior to initiation of treatment with OJEMDA. (2.1)
- Recommended dosage of OJEMDA is based on body surface area (see Tables 1 and 2). (2.3)
- Administer OJEMDA orally, once weekly, with or without food. (2.3, 2.4).
- Tablets: Swallow tablets whole with water. Do not chew, cut, or crush. (2.4)
- For Oral Suspension: See full prescribing information for preparation and administration instructions. (2.4)

3 DOSAGE FORMS AND STRENGTHS

Tablets: 100 mg (3)
For Oral Suspension: 25 mg/mL (3)

4 CONTRAINDICATIONS

None. (4)

5 WARNINGS AND PRECAUTIONS

- Hemorrhage: Major hemorrhagic events can occur during treatment with OJEMDA. Withhold, resume at reduced dose, or permanently discontinue based on severity. (5.1)
- Skin Toxicity Including Photosensitivity: Advise patients to monitor for new or worsening skin reactions. Advise patients to limit direct ultraviolet exposure and use precautionary measures such as sunscreen, sunglasses and/or protective clothing during treatment with OJEMDA. Withhold, reduce the dose or permanently discontinue based on severity. (5.2)
- Hepatotoxicity: OJEMDA can cause hepatotoxicity. Monitor liver function tests prior to administration and during treatment. Withhold, reduce the dose or permanently discontinue based on severity. (5.3)
- Effect on Growth: Reductions in growth velocity have been reported. Routinely monitor growth in pediatric patients. (5.4)
- Embryo-Fetal Toxicity: Can cause fetal harm. Advise of the potential risk to a fetus and to use effective nonhormonal contraception. (5.5, 8.1, 8.3)
- NF1 Associated Tumors: Increased tumor growth may occur with OJEMDA. (5.6, 13.2)

6 ADVERSE REACTIONS

The most common adverse reactions (≥30%) were rash, hair color changes, fatigue, viral infection, vomiting, headache, hemorrhage, pyrexia, dry skin, constipation, nausea, dermatitis acneiform, and upper respiratory tract infection. (6.1)

The most common Grade 3 or 4 laboratory abnormalities (≥2%) were decreased phosphate, decreased hemoglobin, increased creatine phosphokinase, increased alanine aminotransferase, decreased albumin, decreased lymphocytes, decreased leukocytes, increased aspartate aminotransferase, decreased potassium, and decreased sodium.

To report SUSPECTED ADVERSE REACTIONS, contact Day One Biopharmaceuticals at toll-free phone # 1-877-204-2820 or FDA at 1-800-FDA-1088 or www.fda.gov/medwatch.

7 DRUG INTERACTIONS

- Moderate and Strong CYP2C8 Inhibitors: Avoid coadministration with OJEMDA. (7.1).
- Moderate and Strong CYP2C8 Inducers: Avoid coadministration with OJEMDA. (7.1).
- Certain CYP3A Substrates: Avoid coadministration of OJEMDA with CYP3A substrates where minimal concentration changes can cause reduced efficacy. (7.2).
- Hormonal contraceptives: Avoid coadministration with OJEMDA. (7.2).

8 USE IN SPECIFIC POPULATIONS

- Lactation: Advise not to breastfeed. (8.2)
- Infertility: May impair fertility in males and females. (8.3)

FULL PRESCRIBING INFORMATION

1 INDICATIONS AND USAGE

OJEMDA is indicated for the treatment of patients 6 months of age and older with relapsed or refractory pediatric low-grade glioma (LGG) harboring a BRAF fusion or rearrangement, or BRAF V600 mutation.

This indication is approved under accelerated approval based on response rate and duration of response [see Clinical Studies (14)]. Continued approval for this indication may be contingent upon verification and description of clinical benefit in a confirmatory trial(s).

2 DOSAGE AND ADMINISTRATION

2.1 Patient Selection

Select patients for treatment with OJEMDA based on the presence of BRAF fusion or rearrangement, or BRAF V600 mutation in tumor specimens [see Clinical Studies (14)].

Information on FDA-approved tests for the detection of BRAF fusions, BRAF rearrangements, and BRAF V600 mutations is available at http://www.fda.gov/companiondiagnostics.

2.2 Recommended Testing Before Initiating OJEMDA

Before initiating OJEMDA, evaluate liver function tests, including ALT, AST and bilirubin [see Warnings and Precautions (5.3)].

2.3 Recommended Dosage

The recommended dosage of OJEMDA based on body surface area (BSA) is 380 mg/m^2 orally once weekly (the maximum recommended dosage is 600 mg orally once weekly) with or without food [see Administration (2.4) and Clinical Pharmacology (12.3)] until disease progression or intolerable toxicity. OJEMDA may be administered as an immediate release tablet (see Table 1) or as an oral suspension (see Table 2). A recommended dosage for patients with BSA less than 0.3 m^2 has not been established.

Table 1 Recommended OJEMDA Tablets Dosage Based on Body Surface Area
Body Surface Area (m^2) | Recommended Dosage
0.30-0.89 | Administer OJEMDA oral suspension once weekly (see Table 2)
0.90-1.12 | 400 mg once weekly
1.13-1.39 | 500 mg once weekly
≥ 1.40 | 600 mg once weekly

Table 2 Recommended Dosage for OJEMDA for Oral Suspension Based on Body Surface Area
Body Surface Area (m^2) | Dose Volume (mL) [OJEMDA for oral suspension has a concentration of 25 mg/mL. Each bottle of OJEMDA for oral suspension delivers 300 mg/12 mL.] | Dosage
0.30-0.35 | 5 | 125 mg once weekly
0.36-0.42 | 6 | 150 mg once weekly
0.43-0.48 | 7 | 175 mg once weekly
0.49-0.54 | 8 | 200 mg once weekly
0.55-0.63 | 9 | 225 mg once weekly
0.64-0.77 | 11 | 275 mg once weekly
0.78-0.83 | 12 | 300 mg once weekly
0.84-0.89 | 14 | 350 mg once weekly
0.90-1.05 | 15 | 375 mg once weekly
1.06-1.25 | 18 | 450 mg once weekly
1.26-1.39 | 21 | 525 mg once weekly
≥1.40 | 24 | 600 mg once weekly

Continue once weekly dosing until disease progression or intolerable toxicity.

2.4 Administration

- Take OJEMDA at a regularly scheduled time once weekly.
- OJEMDA may be taken with or without food [see Clinical Pharmacology (12.3)].

If a dose is missed by:

- 3 days or less, take the missed dose as soon as possible, and take the next dose on its regularly scheduled day.
- more than 3 days, skip the missed dose and take the next dose on its regularly scheduled day.

If vomiting occurs immediately after taking a dose, repeat that dose.

OJEMDA tablets

- Swallow tablets whole with water.
- Do not chew, cut, or crush.

OJEMDA for oral suspension

- Prior to first time use of OJEMDA for oral suspension, ensure that caregivers (and if appropriate, patients) read and understand the "Instructions for Use" before preparing, measuring, and administering OJEMDA.

Preparation and Administration

- Reconstitute the powder in each supplied bottle with exactly 14 mL of room temperature water to form the OJEMDA for oral suspension. After reconstitution each mL contains 25 mg of tovorafenib. Product foaming after reconstitution reduces the deliverable volume.
- Each bottle delivers 300 mg of tovorafenib in 12 mL. For doses greater than 300 mg, reconstitute two bottles to achieve the dose. Split the dose as equally as possible between the two bottles (e.g., 6 mL and 7 mL for a 325 mg dose). Prepare the first bottle and administer dose prior to preparing the second bottle.
- Administer OJEMDA for oral suspension using the supplied oral dosing syringe or feeding tube (minimum 12 French) immediately after preparation.
- If the OJEMDA for oral suspension is not administered within 15 minutes after preparation, instruct the patient to discard it.

2.5 Dosage Modifications for Adverse Reactions

The recommended dosage reductions for adverse reactions for OJEMDA tablets are provided in Table 3 and OJEMDA for oral suspension in Table 4.

Table 3 OJEMDA Tablets: Recommended Dosage Reductions for Adverse Reactions
BSA (m^2) | First Dosage Reduction | Second Dosage Reduction
0.30-1.12 | Administer the oral suspension once weekly (see Table 4)
1.13-1.39 | 400 mg once weekly | Administer OJEMDA oral suspension once weekly (see Table 4)
≥1.40 | 500 mg once weekly | 400 mg once weekly

Table 4 OJEMDA for Oral Suspension: Recommended Dosage Reductions for Adverse Reactions
BSA (m^2) | First Dosage Reduction |  | Second Dosage Reduction
 | Volume (mL) | Dose (mg) | Volume (mL) | Dose (mg)
0.30-0.35 | 4 | 100 mg once weekly | 3 | 75 mg once weekly
0.36-0.42 | 5 | 125 mg once weekly | 4 | 100 mg once weekly
0.43-0.48 | 6 | 150 mg once weekly | 5 | 125 mg once weekly
0.49-0.54 | 7 | 175 mg once weekly | 6 | 150 mg once weekly
0.55-0.63 | 8 | 200 mg once weekly | 6 | 150 mg once weekly
0.64-0.77 | 9 | 225 mg once weekly | 8 | 200 mg once weekly
0.78-0.83 | 10 | 250 mg once weekly | 8 | 200 mg once weekly
0.84-0.89 | 12 | 300 mg once weekly | 10 | 250 mg once weekly
0.90-1.05 | 13 | 325 mg once weekly | 11 | 275 mg once weekly
1.06-1.25 | 15 | 375 mg once weekly | 13 | 325 mg once weekly
1.26-1.39 | 18 | 450 mg once weekly | 15 | 375 mg once weekly
≥1.40 | 20 | 500 mg once weekly | 16 | 400 mg once weekly

The recommended dosage modifications of OJEMDA for adverse reactions are in Table 5.

Table 5 Recommended Dosage Modifications for Adverse Reactions
Severity of ADR [National Cancer Institute Common Terminology Criteria for Adverse Events (NCI CTCAE) version 5.0.] | Dosage Modification [See Table 3 and Table 4 for recommended dosage reductions.]
Hemorrhage [see Warnings and Precautions (5.1)]
- Intolerable Grade 2 - Any Grade 3 | Withhold OJEMDA.; - If improved to Grade 0-1, resume at lower dosage. - If not improved, consider permanent discontinuation of OJEMDA.
- First occurrence of any Grade 4 | Withhold OJEMDA.; - If improved to Grade 0-1, resume at lower dosage.; OR; - Permanently discontinue OJEMDA.
- Recurrent Grade 4 | Permanently discontinue OJEMDA.
Skin Toxicity including Photosensitivity [see Warnings and Precautions (5.2)]
- Intolerable Grade 2 - Grade 3 or 4 | Withhold OJEMDA.; - If improved to Grade 0-1, resume at lower dosage. - If not improved, consider permanent discontinuation of OJEMDA.
Hepatotoxicity [see Warnings and Precautions (5.3)]
- Grade 3 AST or ALT - Grade 3 bilirubin | Withhold OJEMDA. If improved to Grade ≤ 2 or baseline, resume as follows:; - If laboratory abnormality resolves within 8 days, resume OJEMDA at the same dose. - If laboratory abnormality does not resolve within 8 days, resume OJEMDA at lower dosage.
- First occurrence of any Grade 4 | Withhold OJEMDA.; - If improved to Grade 0-1, resume at lower dosage.; OR; - Permanently discontinue OJEMDA
- Recurrent Grade 4 | Permanently discontinue OJEMDA.
Other Adverse Reactions [see Adverse Reactions (6.1)]
- Intolerable Grade 2 - Any Grade 3 | Withhold OJEMDA.; - If improved to Grade 0-1, resume at lower dosage. - If not improved, consider permanent discontinuation of OJEMDA.
- First occurrence of any Grade 4 | Withhold OJEMDA.; - If improved to Grade 0-1, resume at lower dosage.; OR; - Permanently discontinue OJEMDA.
- Recurrent Grade 4 | Permanently discontinue OJEMDA.

3 DOSAGE FORMS AND STRENGTHS

Tablets:

- 100 mg: orange, film-coated, oval tablets debossed with "100"; on one side and "D101" on the opposite side. Each tablet contains 100 mg of tovorafenib.

For Oral Suspension:

- 25 mg/mL: white to off white powder. After reconstitution, each mL of strawberry flavored tovorafenib suspension contains 25 mg of tovorafenib. Each bottle delivers 300 mg of tovorafenib in 12 mL.

4 CONTRAINDICATIONS

None.

5 WARNINGS AND PRECAUTIONS

5.1 Hemorrhage

Hemorrhage, including major hemorrhage defined as symptomatic bleeding in a critical area or organ, can occur with OJEMDA. In the pooled safety population [see Adverse Reactions (6.1)], hemorrhagic events occurred in 37% of patients, including epistaxis in 26% and intratumoral hemorrhage in 9%. Serious events of bleeding occurred in 5% of patients including Grade 5 tumor hemorrhage in 1 patient (0.6%). OJEMDA was permanently discontinued for hemorrhage in 2% of patients.

Advise patients and caregivers of the risk of hemorrhage during treatment with OJEMDA. Monitor for signs and symptoms of hemorrhage and evaluate as clinically indicated. Withhold and resume at reduced dose upon improvement, or permanently discontinue based on severity [see Dosage and Administration (2.5)].

5.2 Skin Toxicity Including Photosensitivity

OJEMDA can cause rash, including maculopapular rash and photosensitivity. In the pooled safety population [see Adverse Reactions (6.1)], rash occurred in 67% of patients treated with OJEMDA, including Grade 3 rash in 12%. Rash resulted in dose interruption in 15% of patients and dose reduction in 7% of patients. OJEMDA was permanently discontinued due to rash in 1% of patients (n=2). In the pooled safety population, dermatitis acneiform occurred in 26% of patients treated with OJEMDA, including Grade 3 dermatitis acneiform in 0.6% of patients (n=1). Dose reduction was required in 2% of patients (n=3) due to dermatitis acneiform.

Monitor for new or worsening skin reactions. Consider dermatologic consultation and initiate supportive care as clinically indicated. Withhold, reduce the dose, or permanently discontinue OJEMDA based on severity of adverse reaction [see Dosage and Administration (2.5)].

Photosensitivity

In the pooled safety population [see Adverse Reactions (6.1)], photosensitivity occurred in 12% of patients treated with OJEMDA, including Grade 3 events in 0.6% of patients (n=1). Advise patients to use precautionary measures against ultraviolet exposure such as use of sunscreen, sunglasses, and/or protective clothing during treatment with OJEMDA. Withhold, reduce the dose, or permanently discontinue OJEMDA based on severity of adverse reaction [see Dosage and Administration (2.5)].

5.3 Hepatotoxicity

OJEMDA can cause hepatotoxicity. In the pooled safety population [see Adverse Reactions (6.1)], increased alanine aminotransferase (ALT) occurred in 42% and increased aspartate aminotransferase (AST) occurred in 74%, including Grade 3 ALT in 4% and increased AST in 2% of patients treated with OJEMDA. The median time to onset of increased ALT or AST was 14 days (range: 3 to 280 days). Increased ALT or AST leading to dose interruption occurred in 5% of patients and dose reductions were required in 1.2% of patients. Increased bilirubin occurred in 23% of patients, including Grade 3 increased bilirubin in 0.6% of patients (n=1) treated with OJEMDA. Hyperbilirubinemia leading to dose discontinuation occurred in a single adult patient with an advanced non-CNS solid tumor.

Monitor liver function tests, including ALT, AST and bilirubin, before initiation of OJEMDA, one month after initiation and then every three months thereafter and as clinically indicated. Withhold and resume at the same or reduced dose upon improvement, or permanently discontinue OJEMDA based on the severity [see Dosage and Administration (2.5)].

5.4 Effect on Growth

OJEMDA can cause reductions in growth velocity. In FIREFLY-1 [see Adverse Reactions (6.1)], treatment-emergent adverse effects on growth were reported in 46% of 133 patients 18 years of age or younger; 35% were Grade 3 or higher. Reduction in growth velocity resulted in dose interruption in 5% of patients, dose reduction in 2.3% of patients, and permanent discontinuation in 3% of patients. The median change from baseline in height percentile was -14 (z-score change -0.6) for evaluable patients on study for 12 months (N=107) and -20 (z-score change -0.9) for evaluable patients on study for 18 months (N=95).

Growth velocity improved after interruption of treatment with OJEMDA. Among 81 evaluable patients, the median annualized growth velocity ranged from 0.86 to 1.8 cm/year during the 2-year treatment period. Of those, 17 patients had height measurements recorded at least 90 days off-treatment and had a 4.2 cm/year median annualized growth velocity. Routinely monitor patient growth during treatment with OJEMDA [see Adverse Reactions (6), Use in Specific Populations (8.4)].

5.5 Embryo-Fetal Toxicity

Based on findings from animal studies and its mechanism of action, OJEMDA may cause fetal harm when administered to a pregnant woman. Tovorafenib was embryo lethal in rats at doses approximately 0.8-fold the human exposure at the recommended dose based on area under the curve (AUC). Advise pregnant women and females of reproductive potential of the potential risk to a fetus. Advise females of reproductive potential to use effective nonhormonal contraception during treatment with OJEMDA and for 28 days after the last dose, since OJEMDA can render some hormonal contraceptives ineffective [see Drug Interactions (7.2)]. Advise male patients with female partners of reproductive potential to use effective contraception during treatment with OJEMDA and for 2 weeks after the last dose [see Use in Specific Populations (8.1, 8.3)].

5.6 NF1 Associated Tumors

Based on nonclinical data in NF1 models without BRAF alterations, tovorafenib may promote tumor growth in patients with NF1 tumors [see Nonclinical Toxicology (13.2)]. Confirm evidence of a BRAF alteration prior to initiation of treatment with OJEMDA.

6 ADVERSE REACTIONS

The following clinically significant adverse reactions are described elsewhere in the labeling:

- Hemorrhage [see Warnings and Precautions (5.1)]
- Skin Toxicity Including Photosensitivity [see Warnings and Precautions (5.2)]
- Hepatotoxicity [see Warnings and Precautions (5.3)]
- Effect on Growth [see Warnings and Precautions (5.4)]

6.1 Clinical Trials Experience

Because clinical trials are conducted under widely varying conditions, adverse reaction rates observed in the clinical trials of a drug cannot be directly compared to rates in the clinical trials of another drug and may not reflect the rates observed in practice.

The safety population described in WARNINGS AND PRECAUTIONS reflects exposure to OJEMDA taken orally once weekly at a dose based on body surface area [see Clinical Studies (14)] in 140 patients with relapsed or refractory pediatric LGG or advanced solid tumors harboring a RAF alteration and a flat dose of 600 mg in 32 adult patients with advanced solid tumors until disease progression or intolerable toxicity. Among 172 patients treated with OJEMDA, 86% were exposed for 6 months or longer and 49% were exposed for 1 year or longer.

Pediatric Low-grade Glioma

The safety of OJEMDA was evaluated in 137 patients with relapsed or refractory pediatric LGG harboring a BRAF alteration in FIREFLY-1 (Arms 1 and 2) [see Clinical Studies (14)]. Patients received OJEMDA at a dose based on body surface area [see Dosage and Administration (2.3] orally once weekly until disease progression or intolerable toxicity.

The median age of patients was 9 years (range 1 to 24 years); 53% male; 58% White, 7% Asian, 2% Black or African American, 6% other races, 25% race was not reported; 2.9% were Hispanic or Latino; and 90% Karnofsky/Lansky performance status of 80 to 100.

Serious adverse reactions occurred in 45% of patients who received OJEMDA. Serious adverse reactions in >2% of patients included viral infection (9%), pneumonia (4%), and sepsis (4%). A fatal adverse reaction of tumor hemorrhage occurred in 1 patient (1%).

Permanent discontinuation of OJEMDA due to an adverse reaction occurred in 7% of patients. Adverse reactions which resulted in permanent discontinuation of OJEMDA in more than one patient were tumor hemorrhage and reduction in growth velocity.

Dosage interruptions of OJEMDA due to an adverse reaction occurred in 57% of patients. Adverse reactions which required dose interruption in ≥5% of patients included rash, pyrexia, vomiting, and hemorrhage.

Dosage reductions of OJEMDA due to an adverse reaction occurred in 24% of patients. Adverse reactions which required dose reduction in ≥2% of patients included rash, and fatigue.

The most common adverse reactions (≥30%) were rash, hair color changes, fatigue, viral infection, vomiting, headache, hemorrhage, pyrexia, dry skin, constipation, nausea, dermatitis acneiform, and upper respiratory tract infection.

The most common Grade 3 or 4 laboratory abnormalities (≥2%) were decreased phosphate, decreased hemoglobin, increased creatine phosphokinase, increased alanine aminotransferase, decreased albumin, decreased lymphocytes, decreased leukocytes, increased aspartate transferase, decreased potassium, and decreased sodium.

Table 6 and Table 7 present adverse reactions and laboratory abnormalities, respectively, identified in FIREFLY-1 (Arms 1 and 2).

Table 6 Adverse Reactions (≥20%) in Patients with Pediatric LGG Who Received OJEMDA in FIREFLY-1 (Arms 1 and 2)
Adverse Reaction | OJEMDA (N=137)
 | All Grades (%) | Grade 3 or 4 (%)
Skin and Subcutaneous Tissue Disorders
Rash [Includes terms erythema multiforme, eczema, rash erythematous, rash macular, rash follicular, rash pruritic, rash maculopapular, rash, rash papular, rash pustular, skin exfoliation, drug eruption, dermatitis, dermatitis bullous.] | 77 | 12
Hair color changes | 76 | 0
Dry skin | 36 | 0
Dermatitis acneiform | 31 | 1
Pruritus | 26 | 1
General Disorders
Fatigue | 55 | 4
Pyrexia | 39 | 4
Edema [Includes terms lip edema, periorbital edema, edema peripheral, localized edema, face edema, vulval edema.] | 26 | 0
Infections and Infestations
Viral infection [Includes terms viral infection, rhinovirus infection, enterovirus infection, viral upper respiratory tract infection, enterocolitis viral, oral herpes, gastroenteritis viral, influenza, influenza like illness, respiratory syncytial virus infection, enterovirus infection, coronavirus infection, COVID-19, SARS-COV-2 test positive, herpes simplex, parainfluenza virus infection, adenoviral upper respiratory infection, viraemia, adenovirus infection, conjunctivitis viral, eye infection viral, metapneumovirus infection, parvovirus infection, respiratory syncytial virus bronchiolitis, respiratory tract infection viral, viral pharyngitis, viral rhinitis, viral tonsillitis.] | 55 | 7
Upper respiratory tract infection | 31 | 1.5
Paronychia | 26 | 1.5
Gastrointestinal Disorders
Vomiting [Includes terms retching, hematemesis.] | 50 | 4
Constipation | 33 | 0
Nausea | 33 | 0
Abdominal pain | 28 | 0
Diarrhea [Includes terms colitis, enterocolitis.] | 22 | 1.5
Stomatitis [Includes terms mouth ulceration, mucosal inflammation, aphthous ulcer, cheilitis.] | 20 | 0
Nervous system disorders
Headache | 45 | 1
Vascular Disorders
Hemorrhage [Includes terms tumor hemorrhage, gastrointestinal hemorrhage, subdural hemorrhage, epistaxis, intracranial tumor hemorrhage, upper gastrointestinal hemorrhage, lower gastrointestinal hemorrhage, vaginal hemorrhage, gingival bleeding, post procedural hemorrhage, hemoptysis, anal hemorrhage.] | 42 | 5 [Includes one Grade 5 event.]

Other clinically important adverse reactions observed in <20% of patients treated with OJEMDA were reductions in growth velocity [see Warnings and Precautions (5.4)] skin discoloration, myalgia, photosensitivity reaction [see Warnings and Precautions (5.2)], and arthralgia.

Table 7 Select Laboratory Abnormalities (≥20%) that Worsened from Baseline in Patients with Pediatric LGG Who Received OJEMDA in FIREFLY-1 (Arms 1 and 2)
Laboratory Abnormality [Severity as defined by National Cancer Institute CTCAE v5.0] | OJEMDA [The denominator for each laboratory parameter is based on the number of patients with a baseline and post-treatment laboratory value available which ranged from 67 to 137 patients.]
Laboratory Abnormality [Severity as defined by National Cancer Institute CTCAE v5.0] | All Grades (%) | Grade 3 or 4 (%)
Hematology
Decreased hemoglobin | 90 | 15
Decreased lymphocytes | 50 | 2
Decreased leukocytes | 31 | 2
Increased lymphocytes | 23 | 0
Chemistry
Decreased phosphate | 87 | 25
Increased AST | 83 | 2
Increased creatine phosphokinase | 83 | 11
Increased LDH | 73 | 0
Decreased potassium | 51 | 2
Increased ALT | 50 | 5
Increased bilirubin | 22 | 1
Decreased albumin | 24 | 5
Decreased sodium | 20 | 2

Increased creatine phosphokinase was a clinically important laboratory abnormality that worsened from baseline in patients treated with OJEMDA.

7 DRUG INTERACTIONS

7.1 Effects of Other Drugs on OJEMDA

Table 8 describes drug interactions where coadministration with another drug affects OJEMDA.

Table 8 Coadministration with Other Drugs that Affect the Use of OJEMDA
Strong or Moderate CYP2C8 Inhibitors
Prevention or Management | - Avoid coadministration of OJEMDA with a strong or moderate CYP2C8 inhibitor.
Mechanism and Clinical Effect(s) | - Tovorafenib is a CYP2C8 substrate. Strong or moderate CYP2C8 inhibitors are predicted to increase tovorafenib exposure based on a mechanistic understanding of its elimination [see Clinical Pharmacology (12.3)], which may increase the risk of adverse reactions with OJEMDA.
Strong or Moderate CYP2C8 Inducers
Prevention or Management | - Avoid coadministration of OJEMDA with a strong or moderate CYP2C8 inducer.
Mechanism and Clinical Effect(s) | - Tovorafenib is a CYP2C8 substrate. Strong or moderate CYP2C8 inducers are predicted to decrease tovorafenib exposure based on a mechanistic understanding of its elimination [see Clinical Pharmacology (12.3)], which may reduce the effectiveness of OJEMDA.

7.2 Effects of OJEMDA on Other Drugs

Table 9 describes drug interactions where coadministration with OJEMDA affects another drug.

Table 9 Coadministration with OJEMDA that Affects the Use of Other Drugs
CYP3A Substrates
Prevention or Management | - Hormonal Contraceptives: Avoid coadministration of hormonal contraceptives with OJEMDA. If coadministration is unavoidable, use an additional effective nonhormonal contraceptive method during coadministration and for 28 days after discontinuation of OJEMDA. - Other CYP3A Substrates: Avoid coadministration of OJEMDA with certain CYP3A substrates where minimal concentration changes may lead to serious therapeutic failures. If coadministration is unavoidable, monitor patients for loss of efficacy unless otherwise recommended in the Prescribing Information for CYP3A substrates.
Mechanism and Clinical Effect(s) | - Tovorafenib is a CYP3A inducer. - Tovorafenib is predicted to decrease exposure of certain CYP3A substrates where minimal concentration changes may lead to serious therapeutic failures [see Clinical Pharmacology (12.3)], which may reduce the effectiveness of these substrates. - Coadministration with hormonal contraceptives (CYP3A substrate) may decrease progestin-x and ethinyl estradiol exposure, which may lead to contraceptive failure and/or an increase in breakthrough bleeding [see Warnings and Precautions (5.5), Use in Specific Populations (8.3)].

8 USE IN SPECIFIC POPULATIONS

8.1 Pregnancy

Risk Summary

Based on findings from animal studies and its mechanism of action [see Clinical Pharmacology (12.1)], OJEMDA can cause fetal harm when administered to a pregnant woman. There are no available data on the use of OJEMDA in pregnant women. Oral administration of tovorafenib to pregnant rats during the period of organogenesis resulted in embryo lethality at exposures 0.8 times the human exposure at the recommended dose based on AUC (see Data). Advise pregnant women of the potential risk to a fetus. In the U.S. general population, the estimated background risk of major birth defects and miscarriage in clinically recognized pregnancies is 2% to 4% and 15% to 20%, respectively.

Data

Animal Data

In an embryo-fetal development study, once daily oral administration of tovorafenib to pregnant rats during the period of organogenesis from gestation days 7 through 17 at doses of 37.5, 75, and 150 mg/kg resulted in early resorptions and total litter loss at all doses. The dose of 37.5 mg/kg/day is approximately 0.8-fold the human exposure at the recommended dose based on AUC.

8.2 Lactation

Risk Summary

There are no data on the presence of tovorafenib or its metabolites in human milk, their effects on the breastfed child, or on milk production. Due to the potential for serious adverse reactions in breastfed children from OJEMDA, advise lactating women not to breastfeed during treatment with OJEMDA and for 2 weeks following the last dose.

8.3 Females and Males of Reproductive Potential

OJEMDA can cause fetal harm when administered to pregnant women [see Use in Specific Populations (8.1)].

Pregnancy Testing

Verify pregnancy status in females of reproductive potential prior to initiating OJEMDA [see Use in Specific Populations (8.1)].

Contraception

Females

Advise females of reproductive potential to use effective nonhormonal contraception during treatment with OJEMDA and for 28 days after the last dose. OJEMDA can render hormonal contraceptives ineffective [see Drug Interactions (7.2)].

Males

Advise male patients with female partners of reproductive potential to use effective contraception during treatment with OJEMDA and for 2 weeks after the last dose.

Infertility

Based on findings in animals, OJEMDA may impact fertility in males and females of reproductive potential. The effects on male animal fertility were reversible. The effects on female animal fertility were not reversible [see Nonclinical Toxicology (13.1)].

8.4 Pediatric Use

The safety and effectiveness of OJEMDA in pediatric patients 6 months of age and older with relapsed or refractory pediatric LGG harboring a BRAF fusion or rearrangement, or BRAF V600 mutation have been established based on data from a multicenter, open-label, single-arm clinical trial [see Clinical Studies (14)].

The efficacy of OJEMDA was evaluated in 76 patients with relapsed or refractory pediatric LGG. The safety of OJEMDA was evaluated in 137 patients with relapsed or refractory pediatric LGG in FIREFLY-1 (Arms 1 and 2). Of these 137 patients, 2% (n=3) were 6 month to < 2 years of age, 67% (n=92) were 2 years to < 12 years of age, and 31% (n=42) were >12 years of age [see Adverse Reactions (6.1)]. Cmax and AUC in pediatric patients aged 11 months to 17 years were within the range of values observed in adults given the same dose per body surface area.

The safety and effectiveness of OJEMDA in patients younger than 6 months of age have not been established.

Effect on Growth

Patients with pediatric LGG treated with OJEMDA for up to 24 months showed reductions from baseline in Z-scores for height compared to age and sex-matched normative data. Among 35 patients who experienced reductions in growth velocity who had hand radiographs taken to assess bone age, there was no evidence of premature closure of the epiphyseal growth plates or advancement of bone age. Patients followed after interruption of treatment with OJEMDA showed recovery of growth and increase in Z-scores. Monitor growth routinely during treatment [see Warnings and Precautions (5.4)].

8.6 Hepatic Impairment

No dose adjustment is recommended for patients with mild (bilirubin ≤ upper limit of normal (ULN) and aspartate aminotransferase (AST) > ULN or bilirubin > 1× to 1.5× ULN and any AST) hepatic impairment. OJEMDA has not been studied in patients with moderate (bilirubin > 1.5× to 3× ULN and any AST) to severe (bilirubin > 3× ULN and any AST) hepatic impairment [see Clinical Pharmacology (12.3)].

8.7 Renal Impairment

No dose adjustment is recommended for patients with mild-to-moderate renal impairment (eGFR ≥ 30 mL/min/1.73 m^2 calculated by Schwartz equation or MDRD equation). OJEMDA has not been studied in patients with severe renal impairment (eGFR <30 mL/min/1.73 m^2) [see Clinical Pharmacology (12.3)].

11 DESCRIPTION

OJEMDA contains tovorafenib, a kinase inhibitor. Tovorafenib has the molecular formula C17H12Cl2F3N7O2S and a molecular weight of 506.29. The chemical name for tovorafenib is 6-amino-5-chloro-N-[(1R)-1-[5-[[[5-chloro-4-(trifluoromethyl)-2-pyridinyl]amino]carbonyl]-2-thiazolyl]ethyl]-4-pyrimidinecarboxamide. Tovorafenib has the following chemical structure:

It is a white to off-white powder. The solubility of tovorafenib at 37ºC is ≤ 3 micrograms/mL from pH 1.2 to 8 in aqueous media.

OJEMDA (tovorafenib) tablets are supplied as 100 mg strength tablets for oral administration. Each tablet contains 100 mg tovorafenib and the following inactive ingredients: copovidone, colloidal silicon dioxide, croscarmellose sodium, magnesium stearate, microcrystalline cellulose, and orange film coating (hypromellose, polyethylene glycol 8000, titanium dioxide, ferric oxide yellow, ferric oxide red).

OJEMDA (tovorafenib) for oral suspension is a white to off white powder which produces a white suspension when reconstituted with water. Each mL of reconstituted tovorafenib suspension contains 25 mg of tovorafenib and the following inactive ingredients: artificial strawberry flavor, colloidal silicon dioxide, copovidone, maltodextrin, mannitol, microcrystalline cellulose, simethicone, sodium lauryl sulfate, and sucralose.

12 CLINICAL PHARMACOLOGY

12.1 Mechanism of Action

Tovorafenib is a Type II RAF kinase inhibitor of mutant BRAF V600E, wild-type BRAF, and wild-type CRAF kinases.

Tovorafenib exhibited antitumor activity in cultured cells and xenograft tumor models harboring BRAF V600E and V600D mutations, and in a xenograft model harboring a BRAF fusion.

12.2 Pharmacodynamics

Exposure Response Relationships

Tovorafenib exposure is associated with reduction in height-for-age z-scores in pediatric patients. Reduced height-for-age risk persists during treatment with tovorafenib.

Higher tovorafenib exposure is associated with increased risk of skin rash, elevated liver enzymes (AST and ALT), and elevated creatine phosphokinase.

The exposure-response relationship for overall response rate based on RAPNO-LGG (Response Assessment in Pediatric Neuro-Oncology), and RANO-LGG (Response Assessment in Neuro-Oncology) were not clinically significant over the dosage range of 290 to 476 mg/m^2 (0.76-1.25 times the approved recommended dosage) [see Dosage and Administration (2.3) and Clinical Studies (14)].

Cardiac Electrophysiology

At the recommended OJEMDA dosage of 380 mg/m^2 orally once weekly (not to exceed 600 mg), a mean increase in the QT interval >20 milliseconds was not observed.

12.3 Pharmacokinetics

Tovorafenib pharmacokinetic parameters are presented as mean (CV%) unless otherwise indicated. Tovorafenib steady state maximum concentration (Cmax) is 6.9 µg/mL (23%) and the area under the concentration-time curve (AUC) is 508 µg*h/mL (31%). Time to reach steady state of tovorafenib is 12 days (33%). Tovorafenib exposure increases in a dose-proportional manner. No clinically significant tovorafenib accumulation occurs.

Absorption

Tovorafenib median (minimum, maximum) time to achieve peak plasma concentration (Tmax) is 3 hours (1.5, 4 hours), following a single dose with tablets or oral suspension.

Effect of Food

No clinically significant differences in tovorafenib Cmax and AUC were observed following administration of tablets with a high-fat meal (approximately 859 total calories, 54% fat) compared to fasted conditions, but the Tmax was delayed to 6.5 hours.

Distribution

Tovorafenib apparent volume of distribution is 60 L/m^2 (23%). Tovorafenib is 97.5% bound to human plasma proteins in vitro.

Elimination

Tovorafenib terminal half-life is approximately 56 hours (33%) and the apparent clearance is 0.7 L/h/m^2 (31%).

Metabolism

Tovorafenib is primarily metabolized by aldehyde oxidase and CYP2C8 in vitro. CYP3A, CYP2C9, and CYP2C19 metabolize tovorafenib to a minor extent.

Excretion

Following a single oral dose of radiolabeled tovorafenib, 65% of the total radiolabeled dose was recovered in the feces (8.6% unchanged) and 27% of the dose was recovered in the urine (0.2% unchanged).

Specific Populations

No clinically significant differences of tovorafenib were observed based on age (range: 1 to 94 years), sex, race (White, Black, Asian), mild hepatic impairment [bilirubin ≤ upper limit of normal (ULN) and AST > ULN or bilirubin > 1 to 1.5× ULN and any AST], and mild-to-moderate renal impairment (eGFR) ≥ 30 mL/min/1.73 m^2 calculated by Schwartz equation or MDRD equation.

Drug Interaction Studies

Clinical Studies and Model-Informed Approaches

CYP3A Substrates: Midazolam (CYP3A4 substrate) steady-state Cmax and AUC are predicted to decrease by at least 20% following coadministration with tovorafenib.

In Vitro Studies

CYP450 Enzymes: Tovorafenib inhibits CYP2C8, CYP2C9, CYP2C19 and CYP3A, but does not inhibit CYP1A2, CYP2B6, and CYP2D6 at clinically relevant concentrations.

Tovorafenib induces CYP3A, CYP2C8, CYP1A2, CYP2B6, CYP2C9 and CYP2C19 at clinically relevant concentrations.

Transporter Systems: Tovorafenib is not a substrate of BCRP, P-glycoprotein (P-gp), OATP1B1 and OATP1B3. Tovorafenib has not been evaluated as a substrate of OAT1, OAT3, MATE1, MATE2-K and OCT2. Tovorafenib inhibits BCRP at clinically relevant concentrations.

13 NONCLINICAL TOXICOLOGY

13.1 Carcinogenesis, Mutagenesis, Impairment of Fertility

Tovorafenib was not carcinogenic in the 6-month study in transgenic rasH2 mice that received oral doses up to 100 mg/kg/day.

Tovorafenib was not mutagenic in the in vitro bacterial reverse mutation (Ames) assay. Tovorafenib was not genotoxic in cultured human lymphocytes without metabolic activation. Tovorafenib induced chromosomal aberrations in cultured human lymphocytes with metabolic activation at a single concentration in vitro. Tovorafenib was not genotoxic in an in vivo rat bone marrow micronucleus assay.

In a fertility and early embryonic development study in rats, animals were administered tovorafenib doses of 37.5, 75, or 150 mg/kg/day orally. Female animals, paired with untreated males, were dosed for 14 days prior to pairing, during the mating period, and up to Gestation Day 6. Tovorafenib decreased the number of pregnancies, corpora lutea, and live embryos, as well as increased post-implantation losses at all doses. The dose of 37.5 mg/kg/day is approximately 0.8-fold the human exposure at the recommended dose based on AUC.

In repeat- dose toxicology studies in rats of up to 3 months duration, tovorafenib-related findings in female rats included reversible increased thickness of the vaginal mucosa, increased size and/or numbers of corpora hemorrhagicum and hemorrhage, and non-reversible cystic follicles, decreased corpora lutea, and interstitial cell hyperplasia were observed in ovaries at doses ≥ 50 mg/kg once every other day (approximately 0.4-fold the human exposure at the recommended dose based on AUC). In male rats, tovorafenib reduced weights of epididymis and testes, which correlated with reversible tubular degeneration/atrophy of the testes and reduced epididymal sperm at doses ≥ 50 mg/kg once every other day (approximately 0.3-fold the human exposure at the recommended dose based on AUC).

13.2 Animal Toxicology and/or Pharmacology

In vitro, tovorafenib increased phosphorylation of ERK at clinically relevant concentrations in cells with neurofibromatosis Type 1-loss of function (NF1-LOF) suggesting activation, rather than inhibition, of the MAP kinase pathway. In an NF1 genetically engineered mouse model of plexiform neurofibroma without BRAF alteration, tovorafenib did not have antitumor activity, and while not statistically significant, an increase in tumor volume was noted in 2/12 mice (approximately 17%).

14 CLINICAL STUDIES

The efficacy of OJEMDA was evaluated in a multicenter, open-label, single-arm clinical trial (FIREFLY-1; NCT04775485). Eligible patients (N=76) were required to have a relapsed or refractory pediatric low-grade glioma (LGG) harboring an activating BRAF alteration based on local laboratory testing. Patients were also required to have at least one measurable lesion as defined by RANO 2010 criteria. All patients had received at least one line of prior systemic therapy and had documented evidence of radiographic progression. Patients with tumors harboring additional activating molecular alteration(s) (e.g., IDH1/2 mutations, FGFR mutations, etc.) or patients with known or suspected diagnosis of neurofibromatosis type 1 (NF1) were excluded.

Patients received OJEMDA approximately 420 mg/m^2 orally once weekly (range: 290 to 476 mg/m^2, 0.76-1.25 times the approved recommended dosage) according to body surface area with a maximum dose of 600 mg until disease progression or unacceptable toxicity. Although the OJEMDA dosages administered in FIREFLY-1 were between 290 mg/m^2 to 476 mg/m^2, the recommended OJEMDA dosage is 380 mg/m^2 orally once weekly because this dosage was determined to be safe and effective for the treatment of patients 6 months of age and older with relapsed or refractory pediatric LGG harboring a BRAF fusion or rearrangement, or BRAF V600 mutation [see Dosage and Administration (2.3)].

Tumor assessments were performed every 12 weeks.

The major efficacy outcome measure was overall response rate (ORR), defined as the proportion of patients with complete response (CR), partial response (PR), or minor response (MR) by blinded independent central review based on RAPNO-LGG (Response Assessment in Pediatric Neuro-Oncology) criteria. Additional efficacy outcome measures were duration of response, time to response, and ORR by independent review based on RANO-LGG (2011) criteria.

The efficacy population included 76 patients who had measurable disease at baseline and who received OJEMDA. The median age was 8.5 years (range 2 to 21 years); 53% were male; 61% White, 7% Asian, 2.6% Black or African American, 3.9% multiple races, 8% other race, 18% where race was not reported; 3.9% were Hispanic or Latino, and 93% had Karnofsky/Lansky performance status of 80 to 100. Patients received a median of 3 prior systemic regimens (range: 1 to 9). Forty-five patients (59%) received prior treatment with a MAP kinase pathway inhibitor. The most common tumor locations were the optic pathway (51%), deep midline structures (12%), brain stem (8%), cerebellum (7%), and cerebral hemisphere (5%). Fifty-six patients (74%) had a KIAA1549:BRAF fusion, twelve patients (16%) had a V600E mutation, and eight patients (11%) had a BRAF alteration classified as "other" including BRAF duplication or BRAF rearrangement. Efficacy results are shown in Table 10.

Table 10 Efficacy Results in FIREFLY-1
Efficacy Parameter | OJEMDA [Efficacy Results Based on RAPNO-LGG criteria in FIREFLY-1] N=76 [At least one measurable lesion at baseline based on RAPNO-LGG criteria.]
Overall Response Rate
ORR (95% CI) [Based on Clopper-Pearson exact confidence interval.] | 53% (41, 64)
Partial Response (PR), n (%) | 29 (38)
Minor Response (MR), n (%) | 11 (14)
Duration of Response (DoR) | N=40
Median (95% CI) [Based on Kaplan-Meier estimate.] , Months | 18 (12.0, 22.8)
% with observed DoR ≥ 12 months | 65%
% with observed DoR ≥ 18 months | 50%
Abbreviations: LGG = low-grade glioma; RAPNO = Response Assessment in Pediatric Neuro-Oncology; CI = confidence interval.

Among responders, the median time to response was 5.4 months (range 1.6, 17.5). In exploratory analyses of BRAF alteration status, the ORR was 53% among patients with BRAF fusion or rearrangement (n=64), and 50% among patients with BRAF V600E mutation (n=12), respectively. In exploratory analyses of prior therapies, the ORR was 51% among patients who had received prior MAPK-targeted therapy (n=45), and 55% among patients who had not received prior MAPK-targeted therapy (n=31).

Based on RANO-LGG (2011) criteria (n=76), the ORR was 54% [95% CI: (42, 65)], including 23 patients with PR and 18 patients with MR.

16 HOW SUPPLIED/STORAGE AND HANDLING

OJEMDA tablets:

100 mg: orange, film-coated, oval tablets debossed with "100" on one side and "D101" on the opposite side and supplied as follows:

Weekly dose | Each carton contains | Each blister card contains | NDC
400 mg | 4 blister cards | four 100 mg tablets | NDC 82950-001-16
500 mg | 4 blister cards | five 100 mg tablets | NDC 82950-001-20
600 mg | 4 blister cards | six 100 mg tablets | NDC 82950-001-24

Store at 20°C to 25°C (68°F to 77°F); excursions permitted between 15°C to 30°C (59°F to 86°F) [see USP Controlled Room Temperature].

Dispense product in the original package. Tablets should not be removed from blister cards until immediately before use.

STORAGE AND HANDLING

OJEMDA for oral suspension:

25 mg/mL: white to off white powder in a clear glass bottle, co-packaged with a press-in bottle adaptor and a 20 mL oral dosing syringe (NDC# 82950-012-01).

Each mL of reconstituted, strawberry flavored tovorafenib suspension contains 25 mg of tovorafenib. Each bottle delivers 300 mg of tovorafenib in 12 mL.

Store at 20°C to 25°C (68°F to 77°F); excursions permitted between 15°C to 30°C (59°F to 86°F) [see USP Controlled Room Temperature].

Do not use if safety seal under cap is broken or missing.

Suspension must be used immediately after reconstitution.

Discard the bottle (including any unused portion) and syringe after dosing.

17 PATIENT COUNSELING INFORMATION

Advise the patient to read the FDA-approved patient labeling (Patient Information and Instructions for Use).

Hemorrhage

Advise patients that OJEMDA can cause bleeding and to contact their healthcare provider for signs or symptoms of bleeding [see Warnings and Precautions (5.1)].

Skin Toxicities

Advise patients that OJEMDA can cause skin toxicities and to contact their healthcare provider for worsening or intolerable rash [see Warnings and Precautions (5.2)].

Photosensitivity

Advise patients that OJEMDA can cause photosensitivity. Advise patients to limit direct ultraviolet exposure during treatment with OJEMDA. Recommend that patients use precautionary measures such as use of sunscreen, sunglasses, and/or protective clothing during treatment with OJEMDA [see Warnings and Precautions (5.2)].

Hepatotoxicity

Advise patients that OJEMDA can cause liver toxicity and to contact their healthcare provider for signs or symptoms of liver dysfunction. Advise patients that serial testing of serum liver tests (ALT, AST, bilirubin) is recommended during treatment with OJEMDA [see Warnings and Precautions (5.3)].

Effect on Growth

Advise patients and caregivers that treatment with OJEMDA may cause a reduction in growth velocity, and that growth will be monitored during treatment with OJEMDA [see Warnings and Precautions (5.4)].

Embryo-Fetal Toxicity

- Advise pregnant women and females of reproductive potential of the potential risk to a fetus [see Warnings and Precautions (5.5), Use in Specific Populations (8.1, 8.3)].
- Advise females to inform their healthcare provider of a known or suspected pregnancy during treatment with OJEMDA.
- Advise females of reproductive potential to use effective nonhormonal contraception during treatment and for 28 days after discontinuation of treatment with OJEMDA.
- Advise male patients with female partners of reproductive potential to use effective nonhormonal contraception during treatment with OJEMDA and for 2 weeks after the last dose.

Lactation

Advise women not to breastfeed during treatment with OJEMDA and for 2 weeks after the last dose of OJEMDA [see Use in Specific Populations (8.2)].

Infertility

Advise males and females of reproductive potential of the potential risk for impaired fertility with OJEMDA [see Nonclinical Toxicology (13.1)].

Dosing and Administration

Inform patients and caregivers on how to take OJEMDA and what to do for missed or vomited doses [see Dosage and Administration (2.4)].

Prior to use of the oral suspension, ensure patients or caregivers receive training on proper dosing, preparation, and administration [see Dosage and Administration (2.4) and Instructions for Use].

Storage

Advise patients not to take the OJEMDA tablets out of the blister card until ready to use.

Discard the bottle (including any unused portion) and syringe after dosing.

OJEMDA is a trademark of Day One Biopharmaceuticals Inc.

© 2025 Day One Biopharmaceuticals, Inc. All rights reserved.

Manufactured for:

Day One Biopharmaceuticals, Inc.
Brisbane CA 94005

Manufactured by (tablets):
Quotient Sciences – Philadelphia LLC
3 Chelsea Parkway, Suite 305
Boothwyn PA 19061

Manufactured by (oral suspension):
Quotient Sciences – Philadelphia LLC
3080 McCann Farm Dr.
Garnet Valley, PA 19060

DAY101-USPI-082025v04

PATIENT INFORMATION

OJEMDA (oh-JEM-dah)
(tovorafenib)
tablets, for oral use

OJEMDA (oh-JEM-dah)
(tovorafenib)
for oral suspension

What is OJEMDA?
OJEMDA is a prescription medicine used to treat certain types of brain tumors (cancers) called gliomas in people 6 months and older:

- that is a pediatric low-grade glioma (LGG), and
- that has come back after previous treatment or has not responded to previous treatment and
- that has a certain type of abnormal BRAF gene.

Your healthcare provider will perform a test to make sure that OJEMDA is right for you.
It is not known if OJEMDA is safe and effective in children younger than 6 months of age.

Before taking or giving OJEMDA, tell your healthcare provider about all of your or your child's medical conditions, including if you:

- have bleeding problems
- have skin problems
- have liver problems
- are pregnant or plan to become pregnant. OJEMDA can harm your unborn baby.
  Females who are able to become pregnant:
  - Your healthcare provider will do a test to see if you are pregnant before starting treatment with OJEMDA.
  - You should use effective nonhormonal birth control (contraception) during treatment with OJEMDA and for 28 days after your last dose of OJEMDA.
  - Birth control methods that contain hormones (such as birth control pills, injections, or transdermal systems) may not work as well during treatment with OJEMDA and you could become pregnant. You should use another nonhormonal, effective method of birth control during treatment with OJEMDA.
  - Talk to your healthcare provider about birth control methods that may be right for you during this time.
  - Tell your healthcare provider right away if you become pregnant or think you might be pregnant during treatment with OJEMDA.
  Males with female partners who are able to become pregnant should use effective nonhormonal birth control (contraception) during treatment with OJEMDA and for 2 weeks after your last dose of OJEMDA.
- are breastfeeding or plan to breastfeed. It is not known if OJEMDA passes into your breast milk. Do not breastfeed during treatment and for 2 weeks after your last dose of OJEMDA. Talk to your healthcare provider about the best way to feed your baby during this time.

Tell your healthcare provider about all the medicines you take, including prescription and over-the-counter medicines, vitamins, and herbal supplements.
Taking certain other medicines can affect how OJEMDA works and may increase your risk of side effects. OJEMDA may also affect how other medicines work.
Know the medicines you take. Keep a list of them to show your healthcare provider and pharmacist when you get any new medicine.

How should I take or give OJEMDA?

- Take or give OJEMDA exactly as your healthcare provider tells you to. Do not change your or your child's dose or stop taking OJEMDA unless your healthcare provider tells you.
- Your healthcare provider may change your or your child's dose of OJEMDA, temporarily stop, or completely stop your treatment with OJEMDA if you develop certain side effects.
- Your healthcare provider will either prescribe you or your child OJEMDA tablets or OJEMDA for oral suspension.
- Take or give OJEMDA 1 time each week.
- Take or give OJEMDA with or without food.
- If you miss a weekly dose of OJEMDA by:
  - 3 days or less, take or give the missed dose as soon as you remember. Take or give the next dose of OJEMDA on the next regularly scheduled day.
  - more than 3 days, skip the missed dose and take or give the next dose of OJEMDA on the next regularly scheduled day.
- If vomiting happens right after taking a dose of OJEMDA, take or give the dose again. If you are not sure if you should take or give another dose, contact your healthcare provider.

OJEMDA tablets:

- Swallow tablets whole with water. Do not chew, cut, or crush the tablets.

OJEMDA for oral suspension:

- See the Instructions for Use for instructions on how to prepare, measure and take or give a dose of OJEMDA for oral suspension. If you have any questions, talk to your healthcare provider or pharmacist.
- The OJEMDA oral suspension can be taken or given by mouth, or through a feeding tube (minimum 12 French).
- Your or your child's dose may require preparing 2 bottles of OJEMDA for oral suspension.

What should I avoid while taking OJEMDA?

Limit the amount of time you spend in sunlight. OJEMDA can make your skin sensitive to the sun (photosensitivity). Use sun protection measures, such as sunscreen, sunglasses and wear protective clothes that cover your skin during your treatment with OJEMDA.

What are the possible side effects of OJEMDA?
OJEMDA may cause serious side effects, including:

- bleeding problems (hemorrhage) are common during treatment with OJEMDA and can also be serious. Tell your healthcare provider if you develop any signs or symptoms of bleeding, including:
  - headache, dizziness or feeling weak
  - coughing up blood or blood clots
  - vomiting blood or your vomit looks like "coffee grounds"
  - red or black stools that look like tar
- skin reactions, including sensitivity to sunlight (photosensitivity). OJEMDA can cause skin reactions that can become severe. Tell your healthcare provider if you get new or worsening skin reactions, including:

- rash
- bumps or tiny papules
- acne

- peeling, redness, or irritation
- blisters

See "What should I avoid while taking OJEMDA?"

- liver problems. Your healthcare provider will do blood tests to check your liver function before and during treatment with OJEMDA. Tell your healthcare provider right away if you develop any of the following symptoms:

- yellowing of your skin or your eyes
- dark or brown (tea-colored) urine
- nausea or vomiting
- loss of appetite

- feeling tired
- bruising
- bleeding
- pain in your upper right stomach area

- slowed growth in children. Growth will be checked routinely during treatment with OJEMDA.

The most common side effects of OJEMDA include:

- rash
- hair color changes
- feeling tired
- viral infection
- vomiting
- headache

The most common severe abnormal blood tests include:

- fever
- dry skin
- constipation
- nausea
- acne
- upper respiratory tract infection

- decreased phosphate
- decreased red and white blood cells
- increased creatine phosphokinase
- increase in liver function test

- decreased albumin
- decreased potassium
- decreased sodium

OJEMDA may cause fertility problems in males and females, which may affect your ability to have children. Talk to your healthcare provider if this is a concern for you.
These are not all the possible side effects of OJEMDA.
Call your doctor for medical advice about side effects. You may report side effects to FDA at 1-800-FDA-1088.
You may also report side effects to Day One Biopharmaceuticals at 1-877-204-2820.

How should I store OJEMDA?
OJEMDA tablets:

- Store OJEMDA tablets at room temperature between 68˚F to 77˚F (20˚C to 25˚C).
- Keep OJEMDA tablets in its original package. Tablets should not be removed from blister cards until right before use.

OJEMDA for oral suspension:

- Store the glass bottle containing OJEMDA for oral suspension at room temperature between 68˚F to 77˚F (20˚C to 25˚C).
- Do not use OJEMDA for oral suspension if the safety seal under the cap is broken or missing.
- Throw away your bottle(s), including any unused or expired OJEMDA for oral suspension, and oral dosing syringe after taking or giving a dose.

Keep OJEMDA and all medicines out of the reach of children.

General information about the safe and effective use of OJEMDA.
Medicines are sometimes prescribed for purposes other than those listed in a Patient Information leaflet. Do not use OJEMDA for a condition for which it was not prescribed. Do not give OJEMDA to other people, even if they have the same symptoms that you have. It may harm them. You can ask your pharmacist or healthcare provider for more information about OJEMDA that is written for health professionals.

What are the ingredients in OJEMDA?
Active ingredient: tovorafenib
Inactive ingredients:
Tablet: copovidone, colloidal silicon dioxide, croscarmellose sodium, magnesium stearate, microcrystalline cellulose, and orange film coating (hypromellose, polyethylene glycol 8000, titanium dioxide, ferric oxide yellow, ferric oxide red).
For oral suspension: artificial strawberry flavor, colloidal silicon dioxide, copovidone, maltodextrin, mannitol, microcrystalline cellulose, simethicone, sodium lauryl sulfate, and sucralose.

Manufactured for:
Day One Biopharmaceuticals, Inc.,
Brisbane CA 94005
For more information, go to www.OJEMDA.com or call 1-855-DAY-1BIO (1-855-329-1246).
© 2025 Day One Biopharmaceuticals, Inc. All rights reserved. OJEMDA is a trademark of Day One Biopharmaceuticals Inc.

This Patient Information has been approved by the U.S. Food and Drug Administration.
DAY101-PPI-082025v04

Revised: 08/2025

INSTRUCTIONS FOR USE
OJEMDA (oh-JEM-dah)
(tovorafenib)
for oral suspension

This Instructions for Use contains information on how to prepare, measure, and take or give a dose of OJEMDA for oral suspension.

Important information you need to know before preparing, measuring, and taking or giving a dose of OJEMDA for oral suspension.

- Read this Instructions for Use carefully before you prepare, measure, and take or give a dose of OJEMDA for oral suspension for the first time and each time you get a refill. There may be new information. This information does not take the place of talking with your or your child's healthcare provider about your or your child's medical treatment or condition.
- Your healthcare provider or pharmacist should show you how to prepare, measure, and take or give a dose of OJEMDA for oral suspension correctly. Talk to your healthcare provider or pharmacist if you have questions.
- Take or give OJEMDA for oral suspension exactly as your healthcare provider tells you to.
- You will receive the OJEMDA prescription in a box that contains a bottle with powder, a 20 mL oral dosing syringe, and a bottle adaptor. Contact your healthcare provider or pharmacist if you do not have one or more of these items.
- The bottle is made of glass. Do not use the bottle if it is broken or damaged. Contact your healthcare provider or pharmacist for a new bottle.
- Check the expiration date on the bottle and box. Contact your pharmacist if the expiration date has passed. Expired or unused product can be thrown away (disposed of) in your household trash.
- Only use room temperature water for preparing OJEMDA for oral suspension.
- Each dose of OJEMDA for oral suspension must be given within 15 minutes after the medicine has been prepared.
- Each bottle of OJEMDA for oral suspension is for single use only.
- See "How to throw away used bottles, expired or unused OJEMDA for oral suspension, and oral dosing syringes?" at the end of this Instructions for Use.

The OJEMDA box contains:

Included in the box:

Not included in the box:

- 1 empty clean cup
- room temperature water
- ENFIT syringe and ENFIT adaptor (if taking or giving OJEMDA oral suspension through a feeding tube)

- Always use the oral dosing syringe provided to make sure that you correctly measure your prescribed dose.
- The 20 mL oral dosing syringe is marked to help you correctly measure your prescribed dose of OJEMDA for oral suspension. The barrel of the oral dosing syringe has markings in milliliters (mL).
- Add exactly 14 mL of room temperature water to the bottle to prepare the OJEMDA for oral suspension. Only 12 mL of OJEMDA oral suspension will be taken or given from each prepared bottle.

Note: Your prescribed dose of OJEMDA for oral suspension may require preparing 2 bottles of the powder to give your prescribed dose of OJEMDA for oral suspension. If 2 bottles are required:

- always add exactly 14 mL of room temperature water to each bottle, and
- prepare, take or give the dose of OJEMDA for oral suspension from the first bottle and then repeat the same steps to prepare, take or give the dose of OJEMDA for oral suspension from the second bottle.

- OJEMDA for oral suspension can be taken or given by mouth using the 20 mL oral dosing syringe, or through a feeding tube with a minimum size of 12 French using an ENFIT syringe.
  - If you are taking or giving OJEMDA for oral suspension by mouth, follow Section A, Steps 1 to 19.
  - If taking or giving OJEMDA for oral suspension by a feeding tube, follow Section B, Steps 20 to 25.

Section A: Preparing, measuring, and taking or giving a dose of OJEMDA for oral suspension

Step 1. Wash and dry your hands before preparing, measuring, and taking or giving a dose of OJEMDA for oral suspension.

Step 2. Place your supplies on a clean, flat work surface.

Step 3. Fill a cup half-way with room temperature water. Do not use cold water.

Step 4. Remove air from the oral dosing syringe.
Pull the plunger up into the oral dosing syringe as far as it will go, and then push the plunger back down into the oral dosing syringe as far as it will go. This will help to remove all the air inside.

Step 5. Place the oral dosing syringe tip in the water. Pull up on the plunger to draw water into the oral dosing syringe to the 14 mL mark.
Note: Add exactly 14 ml of water to the bottle with powder.

Step 6. Remove the oral dosing syringe from the cup. Turn the oral dosing syringe tip upward and check for air bubbles.
If large air bubbles appear in the oral dosing syringe, push the water back into the cup and then pull up on the plunger again to draw up the water to the 14 mL mark.
Repeat Step 6 until there are no large air bubbles present. Small air bubbles are ok.
Set the oral dosing syringe aside.

Step 7. Open the bottle with powder by pushing down firmly on the cap and turning it to the left (counter-clockwise).

- Do not throw away the cap.
- Remove the Safety seal.

Do not use the bottle with powder if the safety seal under the cap is broken or missing. Call your healthcare provider or pharmacist if the safety seal is broken.

Step 8. Insert the tip of the oral dosing syringe into the opening of the bottle. Push down on the plunger and inject 14 mL of water into the bottle.

- Remove the tip of the emptied oral dosing syringe from the bottle and set it aside.
- Right away, replace the cap back onto the bottle by pushing down while twisting the cap to the right (clockwise).
- Shake the bottle well for 60 seconds in all directions.

Step 9: Turn bottle upside down to check for any powder stuck to the inside of the bottle.

- If you still see powder in the bottle, continue to shake the bottle for another 15 seconds until you no longer see the powder inside the bottle.
- Do not shake the bottle for more than 2 minutes total time.
- Check the bottle to make sure all of the powder is no longer visible.
- If you still see powder in the bottle, contact your healthcare provider or pharmacist and ask for a new bottle.

Step 10. Turn the bottle upside down again and swirl for 30 seconds.

- Place the bottle on a flat, clean, work surface.
- Remove the cap and check that no solids are stuck in the bottle neck.
- If you see solids in the bottle neck, recap the bottle, turn the bottle upside down, and swirl for an additional 15 seconds.
- Allow the bottle to sit for 60 seconds to allow most of the foam to settle.

Note: Foaming in the bottle will reduce the amount of OJEMDA for oral suspension.

Step 11. Open the bottle by firmly pressing down on the cap and turning it to the left (counterclockwise). Do not throw away the cap.
Firmly insert the bottle adaptor into the bottle by pushing it tightly into the top of the bottle. The top edge of the bottle adaptor should be even with the bottle top.
Do not remove the bottle adaptor after it is inserted into the bottle.

Step 12. Check your or your child's dose in milliliters (mL) as prescribed by your healthcare provider. Pick up the oral dosing syringe again. Each mark on the oral dosing syringe is equal to 1 mL. Draw air into the oral dosing syringe by pulling the plunger out to your prescribed dose. For example, if your prescribed dose is 12 mL, you would draw the oral dosing syringe by pulling the plunger out to the 12 mL mark.

Step 13. Insert the tip of the oral dosing syringe into the bottle adaptor.

- The tip of the oral dosing syringe should fit snugly into the hole of the bottle adaptor.
- Keep the oral dosing syringe attached to the bottle. With the oral dosing syringe in place and holding the bottle where the oral dosing syringe tip inserts into bottle adaptor, swirl the oral suspension for 30 seconds.

Step 14. Inject the air from the oral dosing syringe into the bottle. Hold the oral dosing syringe in place and turn the bottle upside down. To measure the prescribed dose, keep the tip of the oral dosing syringe facing up and pull down on the plunger until the top of the plunger lines up with the prescribed dose in mLs.

Step 15. While the syringe is still in the bottle, remove any air bubbles in the oral dosing syringe by gently pushing the OJEMDA oral suspension back into the bottle and then pulling down on the plunger again to draw up your prescribed dose.
Repeat Step 15 until you see that few or no air bubbles remain or if you draw up the wrong dose in the oral dosing syringe.
Note: Only use up to 12 mL of OJEMDA oral suspension from each prepared bottle.

- If the prescribed dose is more than 12 mL (300 mg), split the dose as equally as possible between each prepared bottle.
- For example, if your dose is 13 mL, draw 6 mL from the first prepared bottle, and 7 mL from the second prepared bottle.

Step 16: Leave the tip of the oral dosing syringe in the bottle adaptor and carefully turn the bottle upright. Put the bottle onto your flat work surface again.
Slowly remove the oral dosing syringe tip from the bottle adaptor by gently pulling straight up. Do not hold the oral dosing syringe by the plunger because the plunger may come out.

Step 17: Check again to be sure the top of the black stopper on the barrel of the oral dosing syringe is at your prescribed mL dose mark. If you do not have the correct prescribed mL dose, repeat Steps 15 to 17.
If you are taking or giving a dose of OJEMDA for oral suspension by mouth, continue to Step 18.
If you are taking or giving a dose of OJEMDA for oral suspension through a feeding tube, go to Section B.
OJEMDA for oral suspension must be given within 15 minutes after prepared for use.

Step 18. You or your child should sit upright to take or give a dose of OJEMDA oral suspension. Place the tip of the oral dosing syringe towards the inside of the cheek in your or your child's mouth.

- Slowly push the medicine into the mouth by pressing down on the plunger.
- Do not forcefully push the plunger. This may cause choking.
- Allow the child to swallow while giving OJEMDA. You or your child may drink liquids right away after swallowing the OJEMDA for oral suspension.
- Be sure to take or give the entire dose of OJEMDA for oral suspension.
- If 2 bottles of OJEMDA for oral suspension are required to take or give your prescribed dose, repeat Section A, Steps 1 to 18 for the second bottle.
- Throw away the prepared OJEMDA for oral suspension if it is not taken or given within 15 minutes.

Step 19: See Section C for instructions on "How to throw away used bottles, expired or unused OJEMDA for oral suspension, and oral dosing syringes"

Section B: Taking or giving a dose of OJEMDA or oral suspension through a feeding tube

Before giving a dose of OJEMDA for oral suspension through a feeding tube, read the following information and talk to your or your child's healthcare provider before continuing to STEP 20:

- OJEMDA for oral suspension may be given through a feeding tube, as directed by your healthcare provider.
- Only use a feeding tube with a minimum size of 12 French.
- Always use the 20 mL oral dosing syringe (included in the box) to prepare each dose of OJEMDA for oral suspension in the bottle.
- Always use a 20 mL ENFIT syringe and an ENFIT adaptor (neither included in the box) to measure and give each dose of OJEMDA for oral suspension through the feeding tube.

Step 20. Flush the feeding tube according to the manufacturer's instructions before giving a dose of OJEMDA for oral suspension.

Step 21: Follow Steps 1 to 11 in Section A to prepare the OJEMDA oral suspension using the 20 mL oral dosing syringe.
Follow Steps 12 to 17 in Section A to draw up your or your child's dose of OJEMDA for oral suspension using the ENFIT syringe and ENFIT adaptor.

Step 22: Connect the 20 mL ENFIT syringe containing OJEMDA for oral suspension to the feeding tube.

Step 23: Apply steady pressure to the plunger to give the entire dose of OJEMDA for oral suspension through the feeding tube.

Step 24: Flush the feeding tube after giving each dose of OJEMDA for oral suspension according to the manufacturer's instructions. If 2 bottles are required, repeat Step 21 and give the remainder of the dose right away.

Step 25: Go to Section C for instructions on "How to throw away used bottles, expired or unused OJEMDA for oral suspension, and oral dosing syringes"

Section C: How to throw away used bottles, expired or unused OJEMDA for oral suspension, and oral dosing syringes

- Throw away your used bottle(s), expired or unused OJEMDA for oral suspension, and oral dosing syringe(s) in your household trash.
- Do not re-use the oral dosing syringe(s).

How should I store OJEMDA?

- Store the glass bottle containing OJEMDA for oral suspension at room temperature between 68˚F to 77˚F (20˚C to 25˚C).

Keep OJEMDA for oral suspension, the oral dosing syringe, and all medicines out of the reach of children.

Manufactured for:
Day One Biopharmaceuticals, Inc.,
Brisbane CA 94005
For more information, go to www.OJEMDA.com or call 1-855-DAY-1BIO (1-855-329-1246).
© 2025 Day One Biopharmaceuticals, Inc. All rights reserved. OJEMDA is a trademark of Day One Biopharmaceuticals Inc.

This Instructions for Use has been approved by the U.S. Food and Drug Administration.

Revised: 08/2025

DAY101-IFU-082025v04

PRINCIPAL DISPLAY PANEL - Kit Carton

NDC 82950-012-01
Rx only

ojemda™
(tovorafenib)
for oral suspension

25 mg/mL

After reconstitution with 14 mL of
water, each bottle delivers a maximum
of 300 mg/12 mL (25mg/mL)
of tovorafenib suspension.

Contents:
1 bottle of OJEMDA
1 oral dosing syringe
1 bottle adapter
1 Instructions for Use

Day One
BIOPHARMACEUTICALS

PRINCIPAL DISPLAY PANEL - 100 mg Tablet Blister Pack Carton

NDC 82950-001-16
Rx only

ojemda™
(tovorafenib) tablets

400 mg Once Weekly Dose
Take four 100-mg tablets once weekly

Oral use

Contains 4 individual weekly
blister cards.

Each blister card contains four
tablets (100 mg per tablet)

16 tablets

Day One
BIOPHARMACEUTICALS